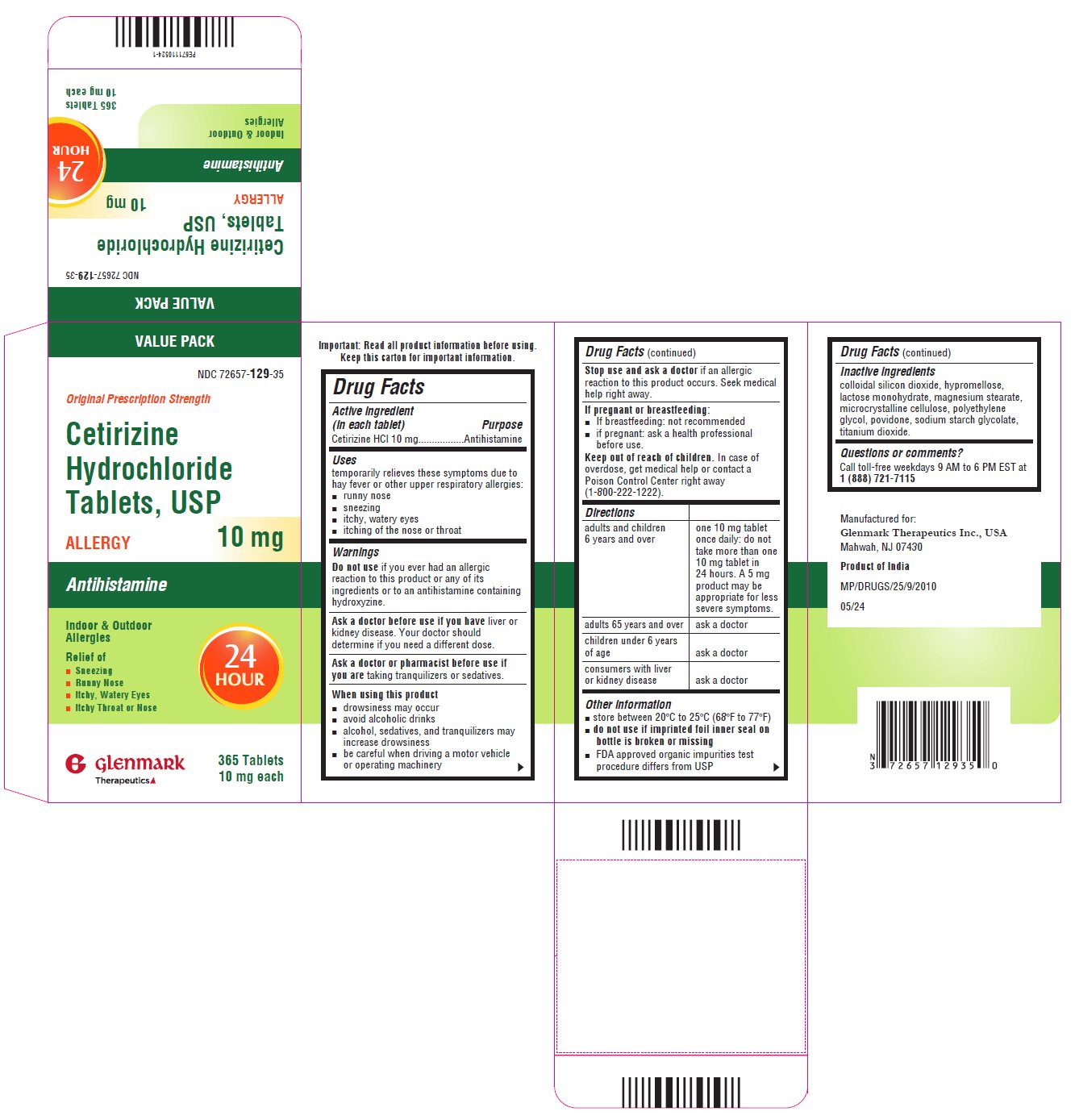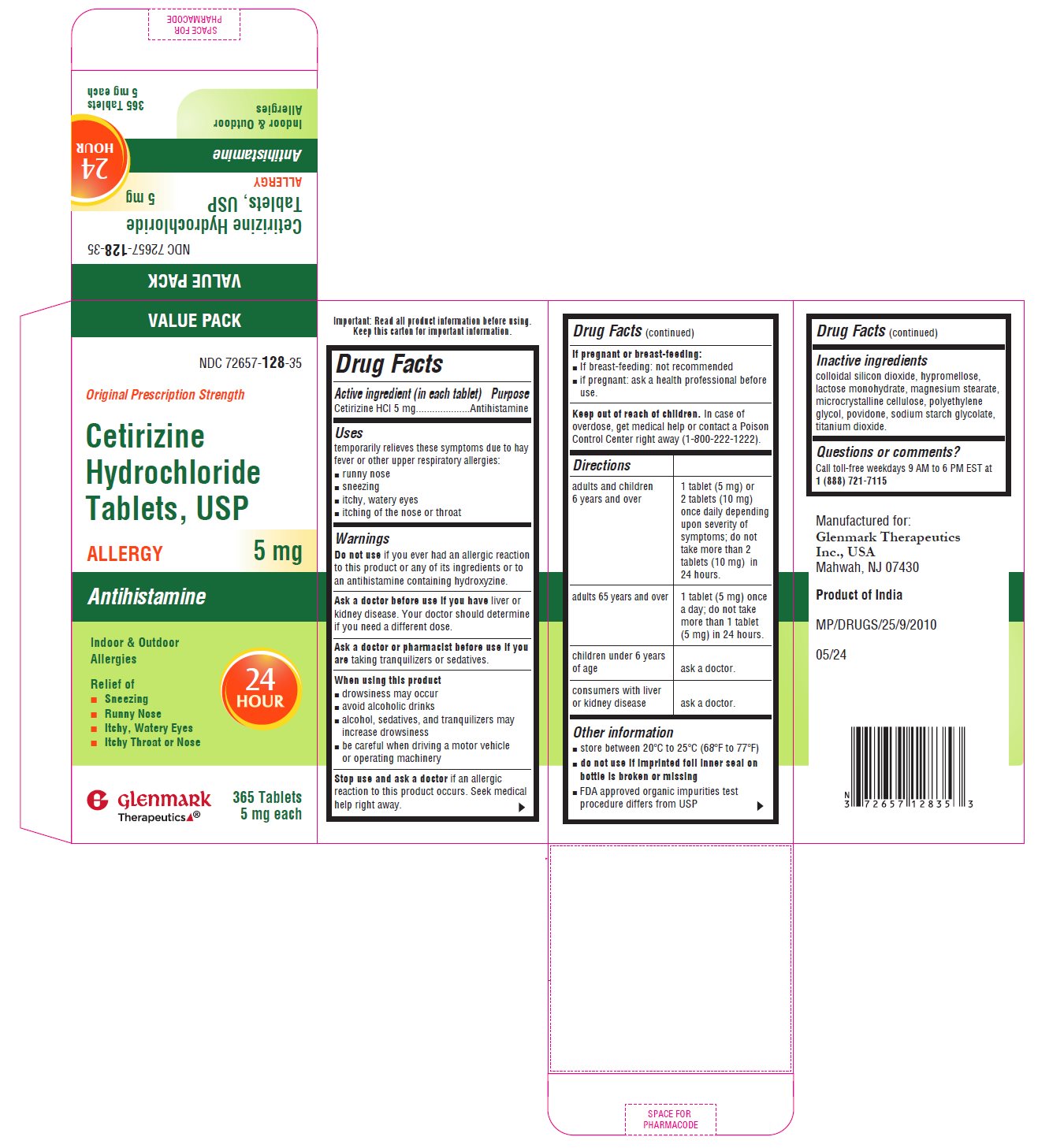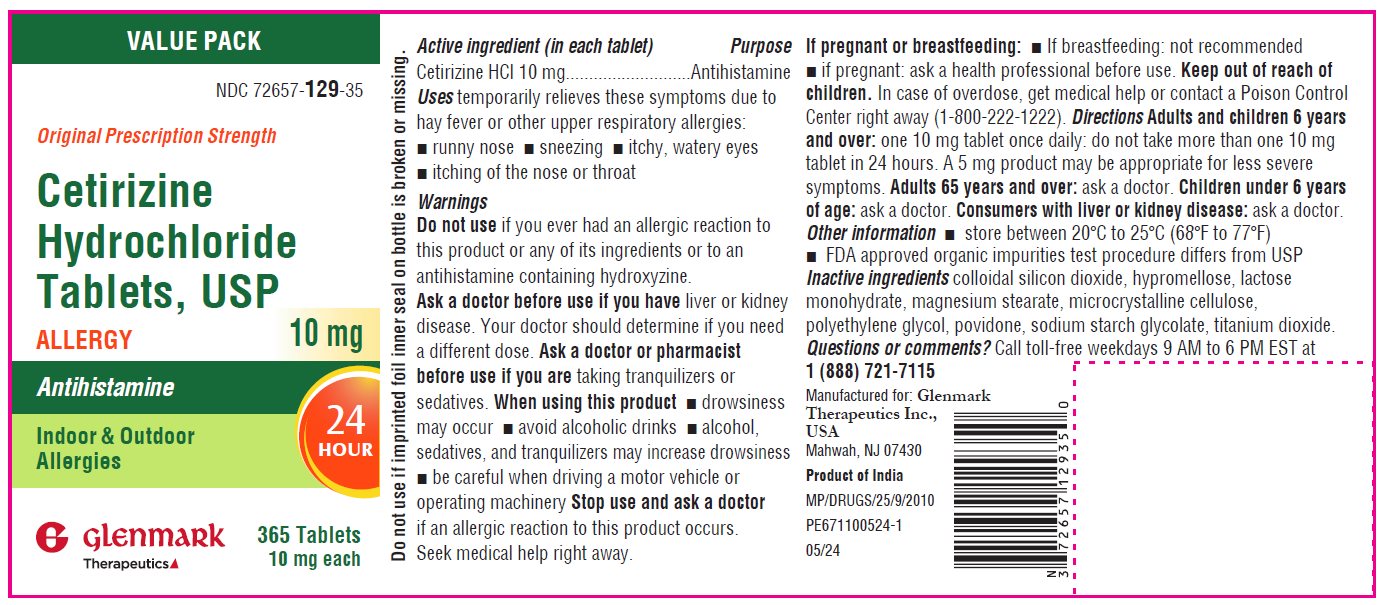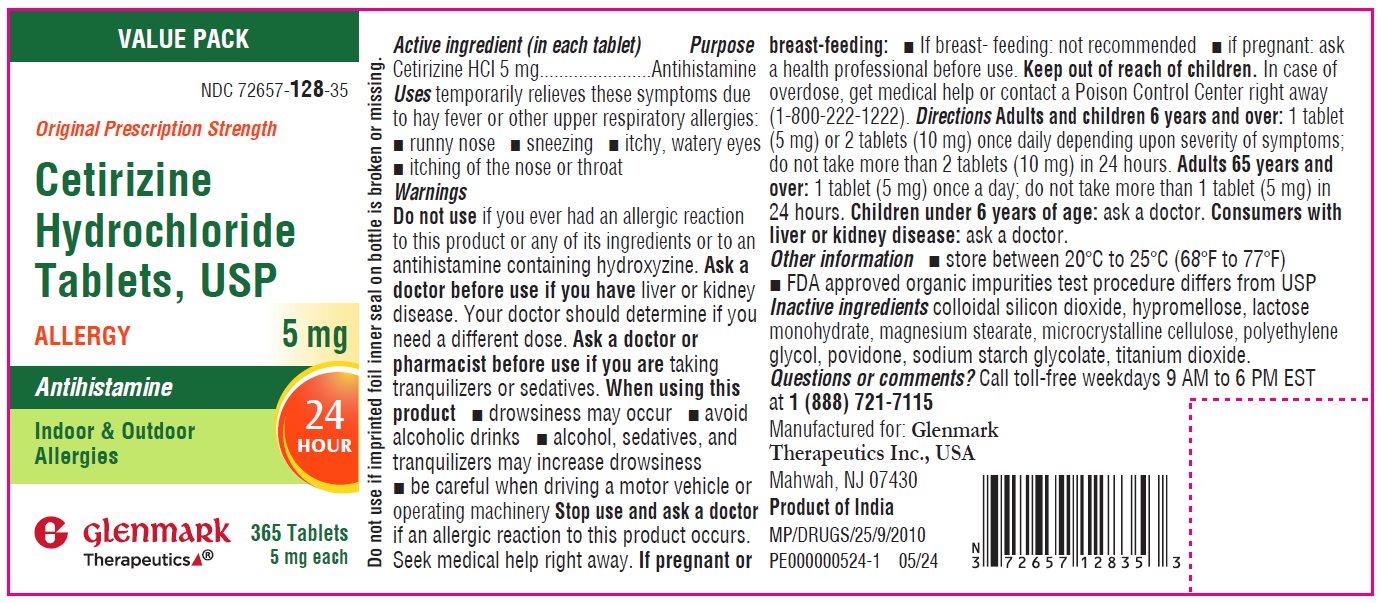 DRUG LABEL: Cetirizine HCl
NDC: 72657-128 | Form: TABLET
Manufacturer: GLENMARK THERAPEUTICS INC., USA
Category: otc | Type: HUMAN OTC DRUG LABEL
Date: 20250421

ACTIVE INGREDIENTS: CETIRIZINE HYDROCHLORIDE 5 mg/1 1
INACTIVE INGREDIENTS: SILICON DIOXIDE; HYPROMELLOSE, UNSPECIFIED; LACTOSE MONOHYDRATE; MAGNESIUM STEARATE; MICROCRYSTALLINE CELLULOSE; POLYETHYLENE GLYCOL, UNSPECIFIED; POVIDONE K30; SODIUM STARCH GLYCOLATE TYPE A; TITANIUM DIOXIDE

Drug Facts

ACTIVE INGREDIENT

Cetirizine HCl 5 mg

Cetirizine HCl 10 mg

PURPOSE

Antihistamine

INDICATIONS AND USAGE

Temporarily relieves these symptoms due to hay fever or other upper respiratory allergies:

- runny nose,
- sneezing,
- itchy, watery eyes,
- itching of the nose or throat

Do not use if you have ever had an allergic reaction to this product or any of its ingredients or an antihistamine containing hydroxyzine

Ask a doctor before useif you have liver or kidney disease.

Your doctor should determine if you need a different dose.

Ask a doctor or pharmacist before use if you are taking tranquilizers or sedatives

When using this product

- drowsiness may occur
- avoid alcoholic drinks
- alcohol, sedatives, and tranquilizers may increase drowsiness
- be careful when driving a motor vehicle or operating machinery

Stop use and ask a doctor if an allergic reaction to this product occurs. Seek medical help right away.

If pregnant or breast-feeding:

- If breast-feeding: not recommended
- if pregnant: ask a health professional before use.

Keep out of reach of children.

In case of overdose, get medical help or contact a Poison Control Center right away (1-800-222-1222)

DOSAGE AND ADMINISTRATION

Cetirizine Hydrochloride Tablets, USP 5 mg

adults and children 6 years and over | 1 tablet (5 mg) or 2 tablets (10) once daily depending upon severity of symptoms; do not take more than 2 tablets (10) in 24 hours.
adults 65 years and over | 1 tablet (5 mg) once a day; do not take more than 1 tablet (5 mg) in 24 hours.
children under 6 years of age | ask a doctor
consumers with liver or kidney disease | ask a doctor

Cetirizine Hydrochloride Tablets, USP 10 mg

adults and children 6 years and over | one 10 mg tablet once daily; do not take more than one 10 mg tablet in 24 hours.; A 5 mg product may be appropriate for less severe symptoms.
adults 65 years and over | ask a doctor
children under 6 years of age | ask a doctor
consumers with liver or kidney disease | ask a doctor

Other information

- store between 20°C to 25°C (68°F to 77°F)
- do not use of imprinted foil inner seal on bottle is broken or missing.
- FDA approved organic impurities test procedure differs from USP

INACTIVE INGREDIENT

colloidal silicon dioxide, croscarmellose sodium, hypromellose, lactose monohydrate, magnesium stearate, microcrystalline cellulose, polyethylene glycol, titanium dioxide

Questions or comments?

call toll-free weekdays 9 AM to 5 PM EST at 1 (888) 721-7115

Manufactured by:

Glenmark Pharmaceuticals Limited

Pithampur, Madhya Pradesh 454775, India

Distributed by:

Glenmark Therapeutics Inc., USA

Mahwah, NJ 07430

Product of India

February 2024

Package/Label Principal Display Panel

Container label

NDC 72657-129-35

10 mg - 365 Tablets

Package/Label Principal Display Panel

NDC 72657-128-35

5 mg- 365 Tablets

Principal Display Panel

Carton label

NDC 72657-129-35

10 mg - 365 Tablets

Principal Display Panel

NDC 72657-128-35

5 mg - 365 Tablets